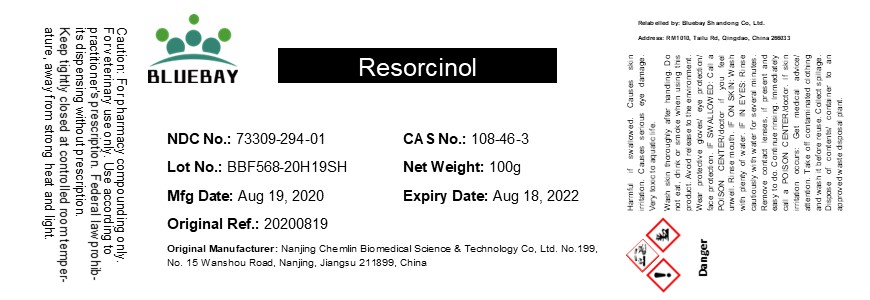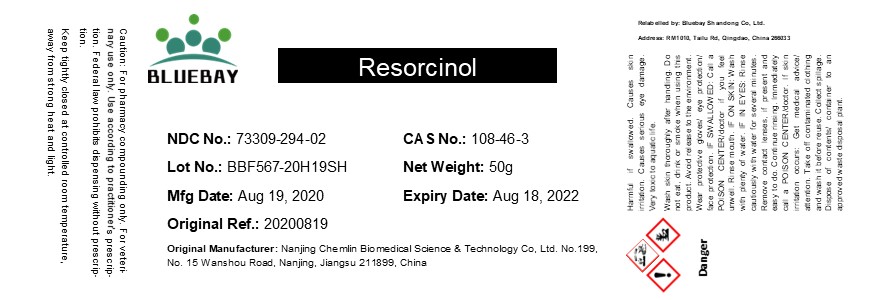 DRUG LABEL: Resorcinol
NDC: 73309-294 | Form: POWDER
Manufacturer: BLUEBAY SHANDONG CO.,LTD
Category: other | Type: BULK INGREDIENT
Date: 20210816

ACTIVE INGREDIENTS: RESORCINOL 1 g/1 g

Resorcinol